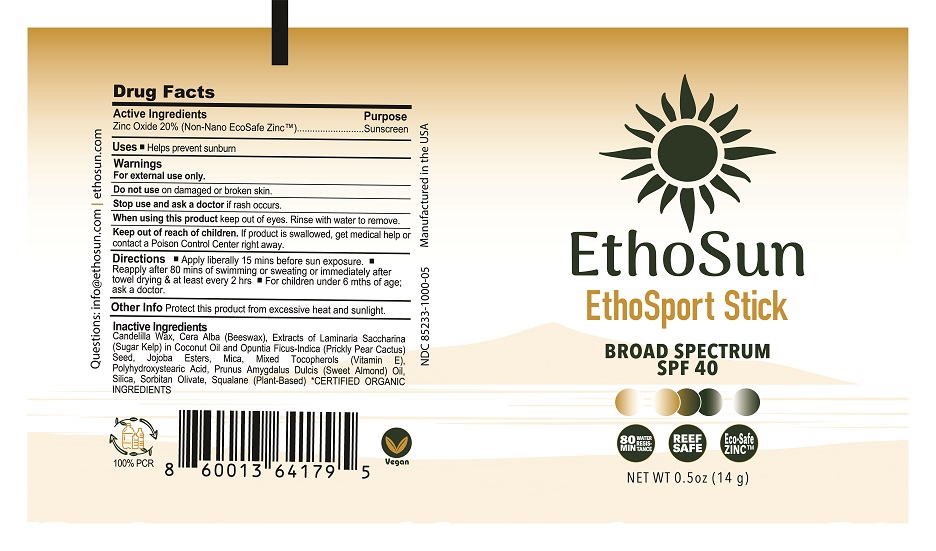 DRUG LABEL: EthoSun EthoSport Stick Broad Spectrum SPF 40
NDC: 85233-1000 | Form: CREAM
Manufacturer: EthoSun, Inc
Category: otc | Type: HUMAN OTC DRUG LABEL
Date: 20250603

ACTIVE INGREDIENTS: ZINC OXIDE 0.2 g/1 [arb'U]
INACTIVE INGREDIENTS: BEESWAX; SILICA; SORBITAN OLIVATE; PRUNUS AMYGDALUS DULCIS (SWEET ALMOND) OIL; HYDROLYZED JOJOBA ESTERS; MICA; TOCOPHEROL; SQUALENE; PRICKLY PEAR FRUIT; CANDELILLA WAX; POLYHYDROXYSTEARIC ACID (2300 MW)

Do not Use

On damaged or broken skin.

Stop use and ask doctor

if rash occurs.

Other Info

Protect product from excessive heat and sun.

Purpose:
Sunscreen

Keep out of reach of children.
If product is swallowed, get medical help or contact a Poison Control Center right away.

Directions:
- Apply liberally 15 minutes before sun exposure.
- Reapply:
• After 80 minutes of swimming or sweating
• Immediately after towel drying
• At least every 2 hours
- For children under 6 months of age: ask a doctor

Inactive Ingredients:
Candelilla Wax, Cera Alba (Beeswax), Extracts of Laminaria Saccharina (Sugar Kelp) in Coconut Oil and Opuntia Ficus-Indica (Prickly Pear Cactus) Seed, Jojoba Esters, Mica, Mixed Tocopherols (Vitamin E), Polyhydroxystearic Acid, Prunus Amygdalus Dulcis (Sweet Almond) Oil, Silica, Sorbitan Olivate, Squalane (Plant-Based)

*CERTIFIED ORGANIC INGREDIENTS

Warnings:
For external use only

Do not use on damaged or broken skin.

Stop use and ask a doctor if rash occurs.

When using this product keep out of eyes. Rinse with water to remove.

Keep out of reach of children. If product is swallowed, get medical help or contact a Poison Control Center right away.

Uses:
Helps prevent sunburn